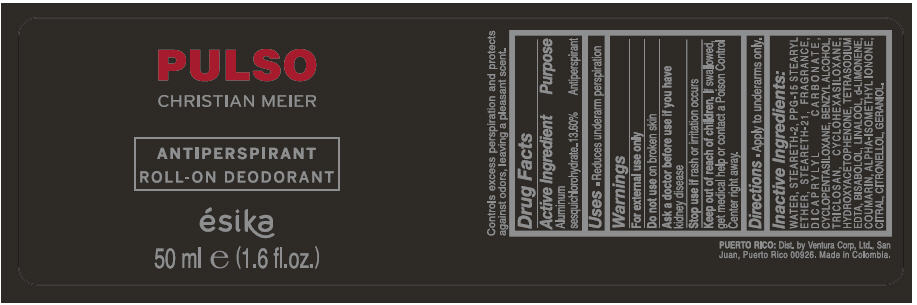 DRUG LABEL: ESIKA PULSO CHRISTIAN MEIER ANTIPERSPIRANT ROLL-ON DEODORANT
NDC: 14141-848 | Form: EMULSION
Manufacturer: Bel Star S.A. (Colombia)
Category: otc | Type: HUMAN OTC DRUG LABEL
Date: 20191116

ACTIVE INGREDIENTS: ALUMINUM SESQUICHLOROHYDRATE 0.136 g/1 mL
INACTIVE INGREDIENTS: WATER; STEARETH-2; PPG-15 STEARYL ETHER; STEARETH-21; DICAPRYLYL CARBONATE; CYCLOMETHICONE 5; BENZYL ALCOHOL; TRICLOSAN; CYCLOMETHICONE 6; EDETATE SODIUM; LEVOMENOL; LINALOOL, (+/-)-; LIMONENE, (+)-; COUMARIN; ISOMETHYL-.ALPHA.-IONONE; CITRAL; .BETA.-CITRONELLOL, (R)-; GERANIOL

ÉSIKA PULSO CHRISTIAN MEIER ANTIPERSPIRANT ROLL-ON DEODORANT

Drug Facts

Active Ingredient

ALUMINUM SESQUICHLOROHYDRATE 13.60%

Purpose

Antiperspirant

Uses

- Reduces underarm perspiration

Warnings

For external use only

Do not use on broken skin

Ask a doctor before use if you have kidney disease

Stop use if rash or irritation occurs

Keep out of reach of children.If swallowed, get medical help or contact a Poison Control Center right away.

Directions

- Apply to underarms only.

Inactive ingredients

WATER, STEARETH-2, PPG-15 STEARYL ETHER, STEARETH-21, FRAGRANCE, DICAPRYLYL CARBONATE, CYCLOPENTASILOXANE, BENZYL ALCOHOL, TRICLOSAN, CYCLOHEXASILOXANE, HYDROXYACETOPHENONE, TETRASODIUM EDTA, BISABOLOL, LINALOOL, d-LIMONENE, COUMARIN, ALPHA-ISOMETHYL IONONE, CITRAL, CITRONELLOL, GERANIOL.

Dist. by Ventura Corp, Ltd., San
Juan, Puerto Rico 00926

PRINCIPAL DISPLAY PANEL - 50 ml Bottle Label

PULSO
CHRISTIAN MEIER

ANTIPERSPIRANT
ROLL-ON DEODORANT

ésika

50 ml e (1.6 fl.oz.)